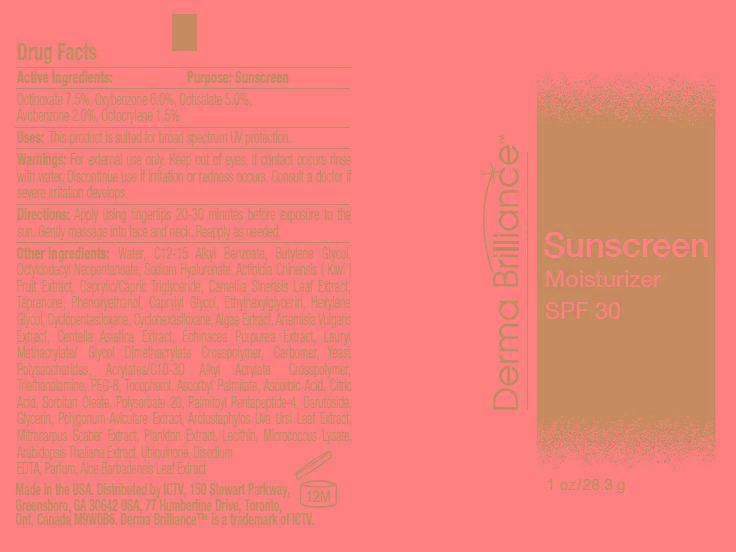 DRUG LABEL: Derma Brilliance Sunscreen SPF 30
NDC: 62742-4073 | Form: CREAM
Manufacturer: Allure Labs, Inc
Category: otc | Type: HUMAN OTC DRUG LABEL
Date: 20150317

ACTIVE INGREDIENTS: OCTINOXATE 7.5 mg/1 g; OXYBENZONE 6 mg/1 g; OCTISALATE 5 mg/1 g; AVOBENZONE 2 mg/1 g; OCTOCRYLENE 1.5 mg/1 g
INACTIVE INGREDIENTS: WATER; ALKYL (C12-15) BENZOATE; BUTYLENE GLYCOL; OCTYLDODECYL NEOPENTANOATE; HYALURONATE SODIUM; KIWI FRUIT; MEDIUM-CHAIN TRIGLYCERIDES; GREEN TEA LEAF; TEPRENONE; PHENOXYETHANOL; CAPRYLYL GLYCOL; ETHYLHEXYLGLYCERIN; HEXYLENE GLYCOL; CYCLOMETHICONE 5; CYCLOMETHICONE 6; ARTEMISIA VULGARIS ROOT; CENTELLA ASIATICA; ECHINACEA PURPUREA; LAURYL METHACRYLATE/GLYCOL DIMETHACRYLATE CROSSPOLYMER; POLYETHYLENE GLYCOL 400; TOCOPHEROL; ASCORBYL PALMITATE; ASCORBIC ACID; CITRIC ACID MONOHYDRATE; SORBITAN MONOOLEATE; POLYSORBATE 20; PALMITOYL PENTAPEPTIDE-4; GLYCERIN; POLYGONUM AVICULARE TOP; ARCTOSTAPHYLOS UVA-URSI LEAF; EGG PHOSPHOLIPIDS; ARABIDOPSIS THALIANA; UBIDECARENONE; EDETATE DISODIUM; ALOE VERA LEAF; Trolamine; CARBOMER COPOLYMER TYPE A (ALLYL PENTAERYTHRITOL CROSSLINKED) 

DRUG FACTS

Active Ingredients:

Octinaxate - 7.5%

Oxybenzone - 6.0%

Octisalate - 5.0%

Avobenzone - 2.0%

Octocrylene - 1.5%

Purpose: Sunscreen

Uses:

- This product is suited for broad spectrum UV protection.

Warnings:

- For external use only.

WHEN USING

- Keep out of eyes.
- If, contacts occurs rinse with water.

Discontinue use if irritation or redness occurs.

Consult a doctor if sever irritation occurs.

Directions:

- Apply using fingertips 20-30 minutes before exposure to the sun.
- Gently massage into face and neck.
- Reapply as needed.

INACTIVE INGREDIENT

Water, Alkyl(C12-15) Benzoate, Butylene Glycol, Octyldodecyl Neopentanoate, Hyaluronate Sodium, Kiwi Fruit, Medium chain Triglycerides, Green Tea Leaf, Teprenone, Phenoxyethanol, Caprylyl Glycol, Ethylhexylglycerin, Hexylene Glycol, Cyclomethicone 5, Cyclomethicone 6, Algae Extract, Artemisia Vulgaris Root, Centella Asiatica, Echinacea Purpurea, Lauryl Methacrylate / Glycol Dimethacrylate, Crosspolymer, Carbomer, Yeast Polysaccharides, Triethanolamine,Acrylate/C10-30 Alkyl Acrylate Crosspolymer, Polyethylene Glycol 400, Tocopherol, Ascorbyl Palmitate, Ascorbic Acid, Citric Acid Monohydrate, Sorbitan Mono Oleate, Polysorbate 20, Palmitoyl Pentapeptide-4, Darutoside, Glycerin, Polygonum Aviculare Top, Arctostaphylos UVA-URSI Leaf, Mitracarpus Scaber Extract, Plankton Extract, Egg Phospholipids, Micrococcus Lysate, Arabidopsis Thaliana, Ubidecarenone, Edetate Disodium, Aloe Vera Leaf.

PACKAGE LABEL

Distributed by:

ICTV, 150 Stewart Parkway,

Greensboro, GA 30642 USA 77 Humberline Drive, Toronto,

Ont, Canada M9W0B6.